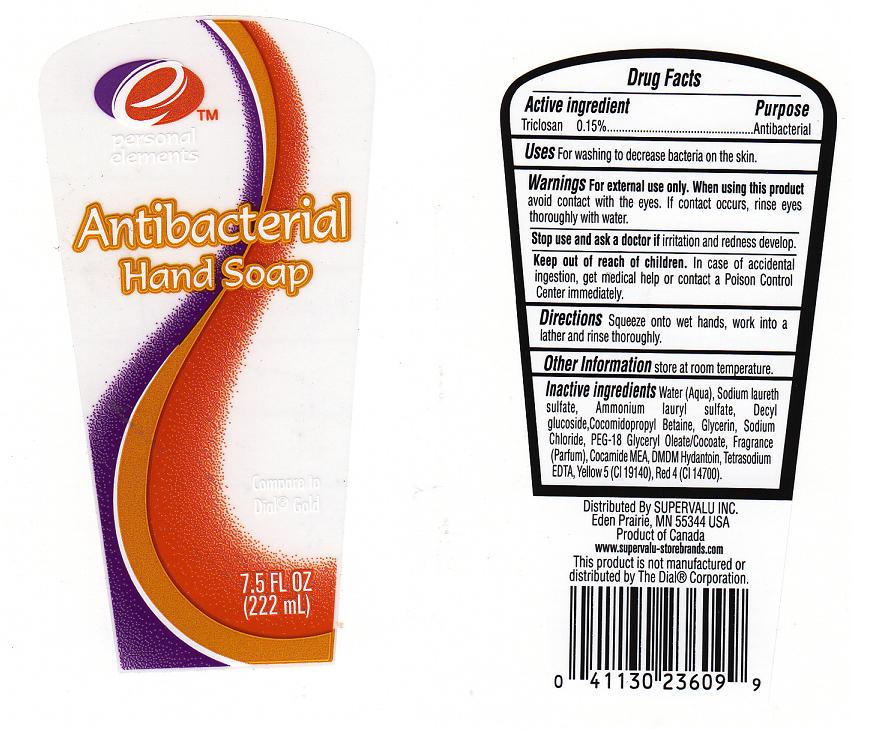 DRUG LABEL: Equaline
NDC: 41163-220 | Form: SOAP
Manufacturer: SUPERVALU INC
Category: otc | Type: HUMAN OTC DRUG LABEL
Date: 20110404

ACTIVE INGREDIENTS: TRICLOSAN 0.15 mL/100 mL
INACTIVE INGREDIENTS: WATER; SODIUM LAURETH SULFATE; AMMONIUM LAURYL SULFATE; COCAMIDOPROPYL BETAINE; GLYCERIN; SODIUM CHLORIDE; COCO MONOETHANOLAMIDE; DMDM HYDANTOIN; EDETATE SODIUM; FD&C YELLOW NO. 5; FD&C RED NO. 4; GLYCERYL MONOOLEATE; LAURYL GLUCOSIDE

DRUG FACTS

ACTIVE INGREDIENT

TRICLOSAN 0.15%

PURPOSE

ANTIBACTERIAL

USES

FOR WASHING TO DECREASE BACTERIA ON THE SKIN.

WARNINGS

FOR EXTERNAL USE ONLY.

WHEN USING THIS PRODUCT AVOID CONTACT WITH THE EYES. IF CONTACT OCCURS, RINSE EYES THROUGHLY WITH WATER.

STOP USE AND ASK A DOCTOR IF

IRRITATION OR REDNESS DEVELOP.

KEEP OUT OF REACH OF CHILDREN

IN CASE OF ACCIDENTAL INGESTION, GET MEDICAL HELP OR CONTACT A POISON CONTROL CENTER IMMEDIATELY.

DIRECTIONS

SQUEEZE ONTO WET HANDS, WORK INTO A LATHER AND RINSE THOROUGHLY.

OTHER INFORMATION

STORE AT ROOM TEMPERATURE

INACTIVE INGREDIENTS

WATER, SODIUM LAURETH SULFATE, AMMONIUM LAURYL SULFATE, DECYL GLUCOSIDE, COCAMIDOPROPYL BETAINE, GLYCERIN, SODIUM CHLORIDE, PEG-18 GLYCERYL OLEATE/COCOATE, FRAGRANCE , COCAMIDE MEA, DMDM HYDANTOIN, TETRASODIUM EDTA, CITRIC ACID,YELLOW 5 (CI 19140), RED 4 (CI 14700).